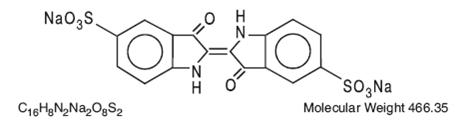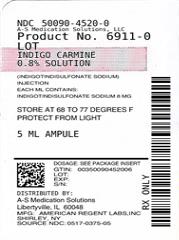 DRUG LABEL: Indigo Carmine
NDC: 50090-4520 | Form: INJECTION, SOLUTION
Manufacturer: A-S Medication Solutions
Category: prescription | Type: HUMAN PRESCRIPTION DRUG LABEL
Date: 20210415

ACTIVE INGREDIENTS: INDIGOTINDISULFONATE SODIUM 8 mg/1 mL
INACTIVE INGREDIENTS: CITRIC ACID MONOHYDRATE; SODIUM CITRATE, UNSPECIFIED FORM; WATER

INDIGO CARMINE INJECTION (Indigotindisulfonate Sodium Injection, USP)

Rx Only

DESCRIPTION

Each mL contains: Indigotindisulfonate Sodium 8 mg, Water for Injection q.s. pH adjusted, when necessary, with Citric Acid and/or Sodium Citrate. Sterile, nonpyrogenic.

Sufficient Indigo Carmine is contained in each 5 mL ampule to permit accurate withdrawal and administration of the full dose. It gives a deep blue solution when dissolved in water.

The structural formula is:

CLINICAL PHARMACOLOGY

Indigo Carmine is excreted largely by the kidneys, retaining its blue color during passage through the body.

Elimination of the dye begins soon after injection, appearing in the urine within 10 minutes in average cases. The biological half-life is 4 to 5 minutes following intravenous injection. Larger quantities are necessary when intramuscular injection is employed. Appearance time and elimination are delayed following intramuscular injection.

INDICATIONS AND USAGE

Originally employed as a kidney function test, the chief application of Indigo Carmine at present is localizing ureteral orifices during cystoscopy and ureteral catheterization.

CONTRAINDICATIONS

Indigo Carmine is contraindicated in patients who have previously experienced an adverse reaction following its use.

WARNINGS

An occasional idiosyncratic drug reaction may occur. A mild pressor effect may be encountered in some patients.

PRECAUTIONS

Pregnancy

Animal Reproduction studies have not been conducted with indigotindisulfonate sodium injection. It is also not known whether indigotindisulfonate sodium injection can cause fetal harm when administered to a pregnant woman or can affect reproduction capacity. Indigotindisulfonate sodium injection should be given to a pregnant woman only if clearly needed.

It is not known whether this drug is excreted in human milk. Because many drugs are excreted in human milk, caution should be exercised when Indigo Carmine is administered to a nursing woman.

ADVERSE REACTIONS

See WARNINGS.

DRUG ABUSE AND DEPENDENCE

Indigo Carmine is not a controlled substance listed in any of the Drug Enforcement Administration Schedules. Its use is not known to lead to dependence or abuse.

OVERDOSAGE

There are no data available describing the signs, symptoms or laboratory findings accompanying overdosage.

No discernible symptoms of toxicity have been observed in mice with an intravenous dose of 200 mg/kg. After intravenous administration the LD50 was established at 300 mg/kg in mice.

DOSAGE AND ADMINISTRATION

Indigo Carmine solution is injected either by the intravenous or intramuscular route, and its appearance at the ureteral orifices is watched with the cystoscope in place. The intravenous method is preferred because a 5 mL injection is sufficient. A lesser dosage in infants, children and underweight patients will prevent skin coloration.

Since precipitation of indigotindisulfonate sodium may occur, Indigo Carmine Solution must not be diluted prior to injection or injected with infusion assemblies which were used with other solutions.

Parenteral drug products should be inspected visually for particulate matter and discoloration prior to administration, whenever solution and container permit.

NOTE: Since Indigo Carmine is a dark blue solution, visual inspection for particulate matter prior to use may not be possible. To ensure that the withdrawn solution contains no particulates, 5 micron filter straws/filter needles must be used when withdrawing contents of ampules^1. The 5 micron nylon mesh filter is suitable for withdrawing the drug product, Indigo Carmine.

^1 ASHP Guidelines on Compounding Sterile Preparations

PROTECT FROM LIGHT. Indigo Carmine should be stored in the dark, away from direct light, preferably in the original package.

Store at 20º to 25º C (68º to 77º F); excursions permitted to 15º to 30º C (59º to 86º F) (See USP Controlled Room Temperature).

HOW SUPPLIED

Product: 50090-4520

NDC: 50090-4520-0 5 mL in a AMPULE